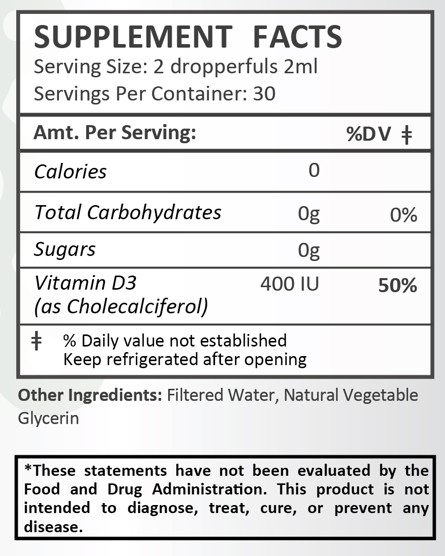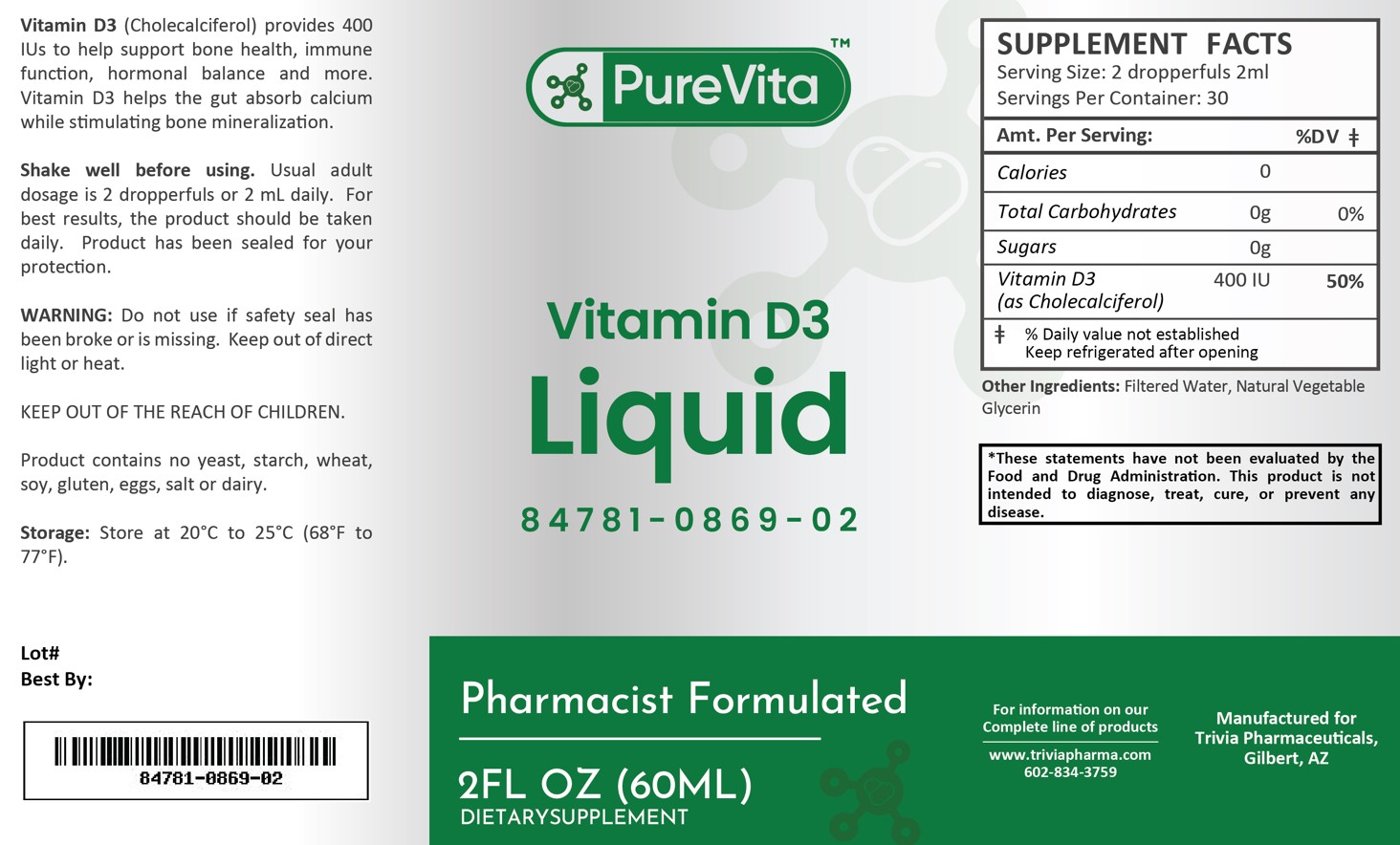 DRUG LABEL: PureVita Vitamin D3
NDC: 84781-869 | Form: LIQUID
Manufacturer: Trivia Pharmaceuticals
Category: other | Type: Dietary Supplement
Date: 20250214

ACTIVE INGREDIENTS: CHOLECALCIFEROL 10 ug/2 mL

PureVita Vitamin D3

Health Claim:

PureVita Vitamin D3 400 iu/2 mL Liquid

Description:

PureVita Vitamin D3 liquid is an orally administered formulation. Vitamin D3 (Cholecalciferol) provides 400 IUs to help support bone health, immune function, hormonal balance and more. Vitamin D3 helps the gut absorb calcium while stimulating bone mineralization.

This listed product is not a National Drug Code, but instead has merely been formatted to comply with standard industry practice for pharmacy and insurance computer systems.

Warnings:

Do not use if safety seal has been broken or is missing. Keep out of direct light or heat.

KEEP OUT OF THE REACH OF CHILDREN.

Product contains no yeast, starch, wheat, soy, gluten, eggs, salt or dairy.

Dosage and Adminsitration:

Usual adult dose is 2 dropperfuls or 2 mL daily. For the best results, the product should be taken daily. Product has been sealed for your protection.

How Supplied:

PureVita Vitamin D3 Liquid is supplied as a clear, white liquid.

84781-0869-02

Reserved for Professional Recommendation

All prescriptions using this product shall be pursuant to state statutes as applicable. This is not an Orange Book product. There are no implied or explicit claims on therapeutic equivalence.

Manufactured for:
Trivia Pharmaceuticals

Gilbert, AZ

Storage:

Storage: Store at 20oC to 25oC (68o F to 77oF). Keep refrigerated after opening.